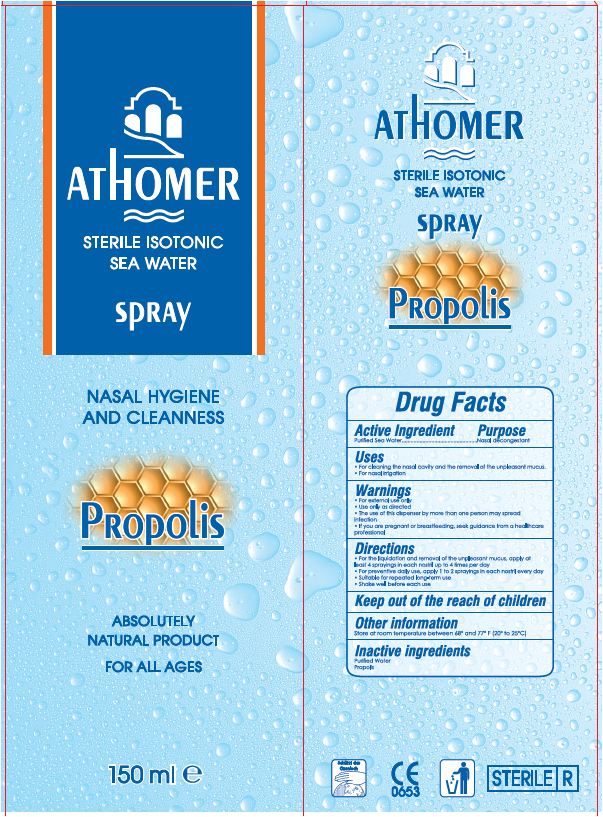 DRUG LABEL: Athomer
NDC: 54753-001 | Form: SPRAY
Manufacturer: PHARMACOSMETIC-DIAFARM
Category: otc | Type: HUMAN OTC DRUG LABEL
Date: 20141104

ACTIVE INGREDIENTS: SODIUM CHLORIDE 0.9 g/100 mL
INACTIVE INGREDIENTS: PROPOLIS WAX; WATER

ATHOMER
STERILE ISOTONIC SEA WATER
SPRAY
PROPOLIS

Drug Facts

Active ingredient
Purified Sea Water

Purpose
Nasal decongestant

Uses

- For cleaning the nasal cavity and the removal of the unpleasant mucus.
- For nasal irrigation

Warnings

- For external use only
- Use only as directed
- The use of this dispenser by more than one person may spread infection
- If you are pregnant or breastfeeding, seek guidance from a healthcare professional

Directions

- For the liquidation and removal of the unpleasant mucus, apply at least 4 sprayings in each nostril up to 4 times per day
- For preventative daily use, apply 1 to 2 sprayings in each nostril every day
- Suitable for repeated long-term use
- Shake well before each use

Keep out of reach of children

Other information

Store at room temperature between 68° and 77° F (20° to 25°C)

Inactive Ingredients

Purified Water
Propolis

PRINCIPAL DISPLAY PANEL - 150 mL carton

ATHOMER

STERILE ISOTONIC
SEA WATER
SPRAY

NASAL HYGIENE
AND CLEANNESS

PROPOLIS

ABSOLUTELY
NATURAL PRODUCT

FOR ALL AGES

150 mL